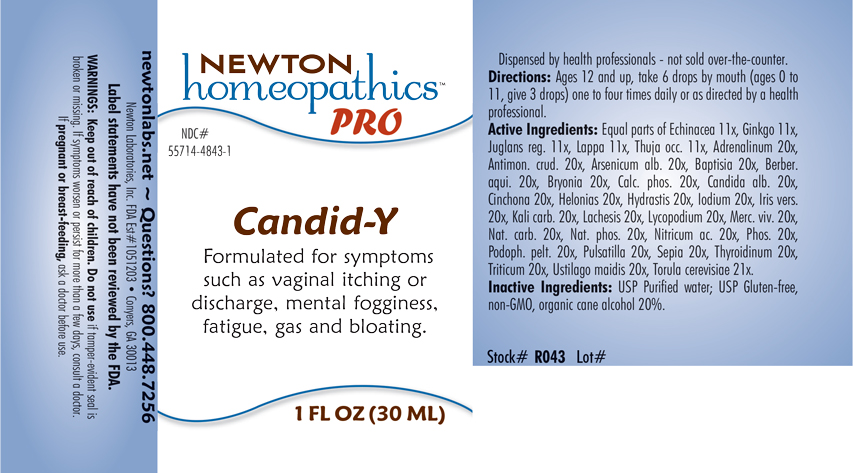 DRUG LABEL: Candid-Y
NDC: 55714-4843 | Form: LIQUID
Manufacturer: Newton Laboratories, Inc.
Category: homeopathic | Type: HUMAN OTC DRUG LABEL
Date: 20210201

ACTIVE INGREDIENTS: GINKGO 11 [hp_X]/1 mL; ENGLISH WALNUT 11 [hp_X]/1 mL; ARCTIUM LAPPA ROOT 11 [hp_X]/1 mL; THUJA OCCIDENTALIS LEAFY TWIG 11 [hp_X]/1 mL; EPINEPHRINE 20 [hp_X]/1 mL; CANDIDA ALBICANS 20 [hp_X]/1 mL; THYROID, UNSPECIFIED 20 [hp_X]/1 mL; SACCHAROMYCES CEREVISIAE 21 [hp_X]/1 mL; ELYMUS REPENS ROOT 20 [hp_X]/1 mL; USTILAGO MAYDIS 20 [hp_X]/1 mL; ANTIMONY TRISULFIDE 20 [hp_X]/1 mL; ARSENIC TRIOXIDE 20 [hp_X]/1 mL; BAPTISIA TINCTORIA 20 [hp_X]/1 mL; MAHONIA AQUIFOLIUM ROOT BARK 20 [hp_X]/1 mL; BRYONIA ALBA ROOT 20 [hp_X]/1 mL; TRIBASIC CALCIUM PHOSPHATE 20 [hp_X]/1 mL; CINCHONA OFFICINALIS BARK 20 [hp_X]/1 mL; CHAMAELIRIUM LUTEUM ROOT 20 [hp_X]/1 mL; GOLDENSEAL 20 [hp_X]/1 mL; IODINE 20 [hp_X]/1 mL; IRIS VERSICOLOR ROOT 20 [hp_X]/1 mL; POTASSIUM CARBONATE 20 [hp_X]/1 mL; LACHESIS MUTA VENOM 20 [hp_X]/1 mL; LYCOPODIUM CLAVATUM SPORE 20 [hp_X]/1 mL; MERCURY 20 [hp_X]/1 mL; SODIUM CARBONATE 20 [hp_X]/1 mL; SODIUM PHOSPHATE, DIBASIC, HEPTAHYDRATE 20 [hp_X]/1 mL; NITRIC ACID 20 [hp_X]/1 mL; SEPIA OFFICINALIS JUICE 20 [hp_X]/1 mL; PHOSPHORUS 20 [hp_X]/1 mL; PODOPHYLLUM 20 [hp_X]/1 mL; ANEMONE PULSATILLA 20 [hp_X]/1 mL; ECHINACEA, UNSPECIFIED 11 [hp_X]/1 mL
INACTIVE INGREDIENTS: WATER; ALCOHOL

Candid-Y 4843L

OTC - KEEP OUT OF REACH OF CHILDREN SECTION

Keep out of reach of children.

OTC - PREGNANCY OR BREAST FEEDING SECTION

If pregnant or breast-feeding, ask a doctor before use.

INACTIVE INGREDIENT SECTION

USP Purified water; USP Gluten-free, non-GMO, organic cane alcohol 20%

OTC - PURPOSE SECTION

Formulated for associated symptoms such as vaginal itching or discharge, mental fogginess, fatigue, gas and bloating.

WARNINGS SECTION

WARNINGS: Keep out of reach of children. Do not use if tamper-evident seal is broken or missing. If symptoms worsen or persist for more than a few days, consult a doctor. If pregnant or breast-feeding, ask a doctor before use.

QUESTIONS SECTION

newtonlabs.net - Questions? 800 448-7256

Newton Laboratories, Inc. FDA Est # 1051203 - Conyers, GA 30013

OTC - ACTIVE INGREDIENT SECTION

Equal parts of Echinacea 11x, Ginkgo 11x, Juglans reg. 11x, Lappa 11x, Thuja occ. 11x, Antimon. crud. 20x, Baptisia 20x, Berber. aqui. 20x, Bryonia 20x, Calc. phos. 20x, Cinchona 20x, Helonias 20x, Hydrastis 20x, Iodium 20x, Iris vers. 20x, Kali carb. 20x, Lachesis 20x, Lycopodium 20x, Merc. viv. 20x, Nat.carb. 20x, Nat. phos. 20x, Nitricum ac. 20x, Phos. 20x, Podoph. pelt. 20x, Pulsatilla 20x, Sepia 20x, Adrenalinum 20x, Arsenium alb. 20x, Candida alb. 20x, Thyroidinum 20x, Triticum 20x, Ustilago maidis 20x, Torula cerevisiae 21x.

DOSAGE & ADMINISTRATION SECTION

Ages 12 and up, take 6 drops by mouth (ages 0 to 11, give 3 drops) one to four times daily or as directed by a health professional.

INDICATIONS & USAGE SECTION

Formulated for associated symptoms such as vaginal itching or discharge, mental fogginess, fatigue, gas and bloating.